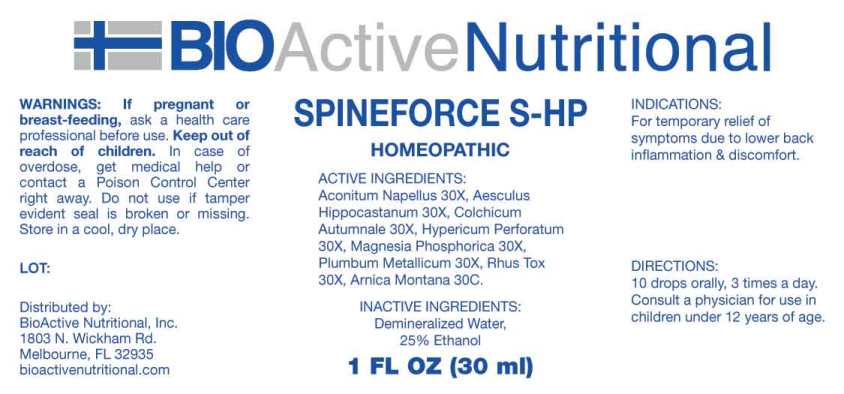 DRUG LABEL: Spineforce S-HP
NDC: 43857-0605 | Form: LIQUID
Manufacturer: BioActive Nutritional, Inc.
Category: homeopathic | Type: HUMAN OTC DRUG LABEL
Date: 20230614

ACTIVE INGREDIENTS: ACONITUM NAPELLUS WHOLE 30 [hp_X]/1 mL; HORSE CHESTNUT 30 [hp_X]/1 mL; COLCHICUM AUTUMNALE BULB 30 [hp_X]/1 mL; HYPERICUM PERFORATUM WHOLE 30 [hp_X]/1 mL; MAGNESIUM PHOSPHATE, DIBASIC TRIHYDRATE 30 [hp_X]/1 mL; LEAD 30 [hp_X]/1 mL; TOXICODENDRON PUBESCENS LEAF 30 [hp_X]/1 mL; ARNICA MONTANA WHOLE 30 [hp_C]/1 mL
INACTIVE INGREDIENTS: WATER; ALCOHOL

DRUG FACTS:

ACTIVE INGREDIENTS:

Aconitum Napellus 30X, Aesculus Hippocastanum 30X, Colchicum Autumnale 30X, Hypericum Perforatum 30X, Magnesia Phosphorica 30X, Plumbum Metallicum 30X, Rhus Tox 30X, Arnica Montana 30C.

INDICATIONS:

For temporary relief of symptoms due to lower back inflammation & discomfort.

WARNINGS:

If pregnant or breast-feeding, ask a health care professional before use.

Keep out of reach of children. In case of overdose, get medical help or contact a Poison Control Center right away.

Do not use if tamper evident seal is broken or missing.

Store in cool, dry place.

Keep out of reach of children. In case of overdose, get medical help or contact a Poison Control Center right away.

DIRECTIONS:

10 drops orally, 3 times a day. Consult a physician for use in children under 12 years of age.

INDICATIONS:

For temporary relief of symptoms due to lower back inflammation & discomfort.

INACTIVE INGREDIENTS:

Demineralized Water, 25% Ethanol

QUESTIONS:

Distributed by:

BioActive Nutritional, Inc.

1803 N. Wickham Rd.

Melbourne, FL 32935

bioactivenutritional.com

PACKAGE LABEL DISPLAY:

BIOActive Nutritional

SPINEFORCE S-HP

HOMEOPATHIC

1 FL OZ (30 ml)